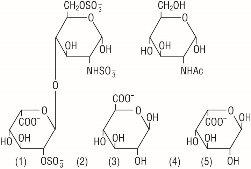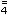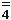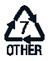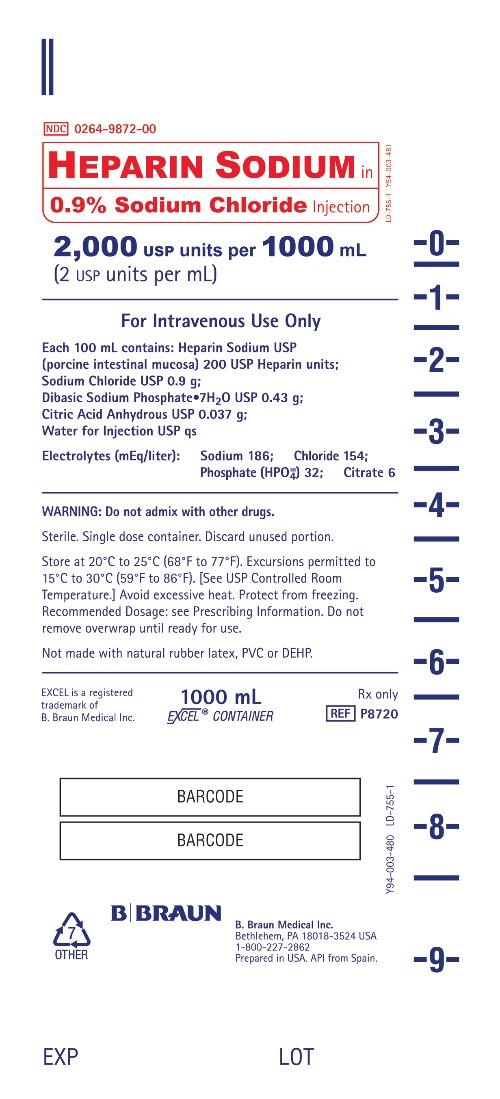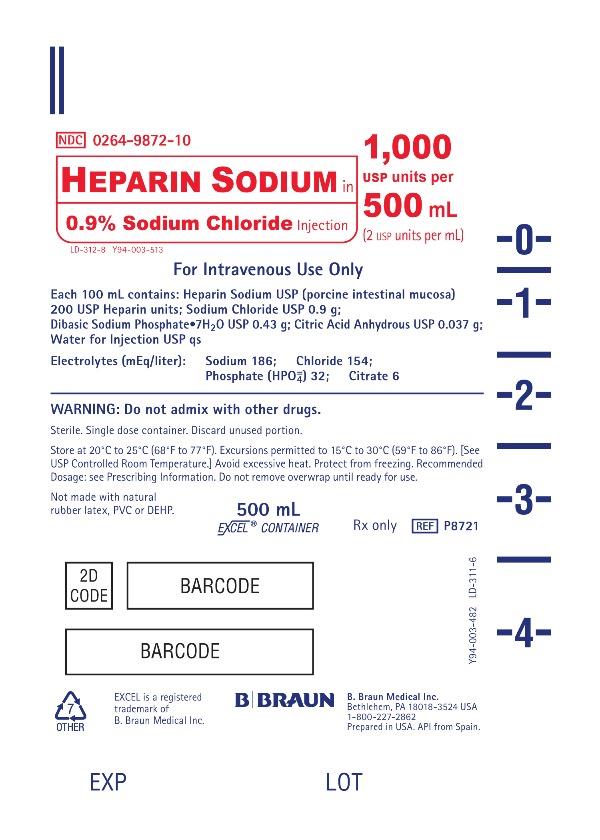 DRUG LABEL: Heparin Sodium in Sodium Chloride
NDC: 0264-9872 | Form: INJECTION
Manufacturer: B. Braun Medical Inc.
Category: prescription | Type: HUMAN PRESCRIPTION DRUG LABEL
Date: 20250806

ACTIVE INGREDIENTS: HEPARIN SODIUM 200 [USP'U]/100 mL
INACTIVE INGREDIENTS: WATER; SODIUM CHLORIDE 0.9 g/100 mL; SODIUM PHOSPHATE, DIBASIC 0.43 g/100 mL; ANHYDROUS CITRIC ACID 0.037 g/100 mL

HIGHLIGHTS OF PRESCRIBING INFORMATION

These highlights do not include all the information needed to use HEPARIN SODIUM IN 0.9% SODIUM CHLORIDE INJECTION safely and effectively. See full prescribing information for HEPARIN SODIUM IN 0.9% SODIUM CHLORIDE INJECTION.
HEPARIN SODIUM IN 0.9% SODIUM CHLORIDE INJECTION, for intravenous use
Initial U.S. Approval: 1939

1 INDICATIONS AND USAGE

HEPARIN SODIUM IN 0.9% SODIUM CHLORIDE INJECTION at the concentration of 2 USP units/mL is an anticoagulant indicated for:

• Maintenance of catheter patency (1)

2 DOSAGE AND ADMINISTRATION

Although the rate of infusion of the 2 USP units/mL formulation is dependent upon the age, weight, clinical condition of the patient, and the procedure being employed, the recommended starting rate is 6 units per hour by intravenous infusion through an intravenous catheter to maintain catheter patency. (2.2)

3 DOSAGE FORMS AND STRENGTHS

- Heparin Sodium 1,000 USP units per 500 mL (2 USP units per mL) in 0.9% Sodium Chloride Injection (3)
- Heparin Sodium 2,000 USP units per 1,000 mL (2 USP units per mL) in 0.9% Sodium Chloride Injection (3)

4 CONTRAINDICATIONS

Heparin Sodium in Sodium Chloride Injection is contraindicated in patients with the following conditions: (4)

- Uncontrollable active bleeding state, except when this is due to disseminated intravascular coagulation (5.2)
- History of heparin-induced thrombocytopenia (HIT) or heparin-induced thrombocytopenia and thrombosis (HITT) (5.3)
- With severe thrombocytopenia (5.3, 5.4)
- Known hypersensitivity to heparin or pork products (5.5, 6.1)

5 WARNINGS AND PRECAUTIONS

- Fatal Medication Errors: Confirm choice of correct strength prior to administration. (5.1)
- Hemorrhage: Fatal cases have occurred. Monitor for signs of bleeding and manage promptly. (5.2)
- HIT or HITT: Monitor for signs and symptoms and discontinue if indicative of HIT or HITT. (5.3)
- Thrombocytopenia: Monitor platelet count during therapy; discontinue heparin in HIT or HITT is suspected. (5.4)
- Hypersensitivity Reactions: Use in patients with prior reactions only in life-threatening situations. (5.5)
- Heparin Resistance: Increased resistance to heparin is frequently encountered in fever, thrombosis, thrombophlebitis, infections with thrombosing tendencies, myocardial infarction, cancer and in postsurgical patients. (5.6)
- Hyperkalemia: Measure plasma potassium in patients at risk of hyperkalemia before starting heparin therapy and periodically in all patients (5.7)
- Elevations of serum aminotransferases: Interpret elevation of these enzymes with caution. (5.8)
- Laboratory Tests: Periodic platelet counts, hematocrits, and tests for occult blood in stool are recommended during the entire course of heparin therapy regardless of the route of administration. (5.9)

6 ADVERSE REACTIONS

Most common adverse reactions are: hemorrhage, thrombocytopenia, HIT or HITT, hypersensitivity reactions, heparin resistance, hyperkalemia, and elevations of aminotransferase levels. (6)

To report SUSPECTED ADVERSE REACTIONS, contact B. Braun Medical Inc. at 1-800-227-2862 or FDA at 1-800-FDA-1088 or www.fda.gov/medwatch.

7 DRUG INTERACTIONS

- Drugs that interfere with platelet aggregation or drugs that counteract coagulation may induce bleeding. (7)

8 USE IN SPECIFIC POPULATIONS

Geriatric Use: A higher incidence of bleeding has been reported in patients over 60 years of age, especially women. (5.2, 8.5)

FULL PRESCRIBING INFORMATION

1 INDICATIONS AND USAGE

Heparin Sodium in 0.9% Sodium Chloride Injection at the concentration of 2 USP units/mL is indicated as an anticoagulant to maintain catheter patency.

2 DOSAGE AND ADMINISTRATION

2.1 Preparation for Administration

Confirm the selection of the correct formulation and strength prior to administration of the drug.

This product should be administered by intravenous infusion only.

Do not use Heparin Sodium in 0.9% Sodium Chloride Injection as a “catheter lock flush” product.

Do not admix with other drugs.

Discard unused portion.

Do not use plastic containers in series connection.

This product should not be infused under pressure.

Parenteral drug products should be inspected visually for particulate matter and discoloration prior to administration, whenever solution and container permit. Use only if solution is clear and container and seals are intact.

2.2 Maintenance of Catheter Patency

Although the rate of infusion of the 2 USP units/mL formulation is dependent upon the age, weight, clinical condition of the patient, and the procedure being employed, the recommended starting rate is 6 units per hour by intravenous infusion through an intravenous catheter to maintain catheter patency.

3 DOSAGE FORMS AND STRENGTHS

HEPARIN SODIUM IN 0.9% SODIUM CHLORIDE INJECTION is a sterile, single-dose, clear, nonpyrogenic solution available as:

- Heparin Sodium 1,000 USP units per 500 mL (2 USP units per mL) in 0.9% Sodium Chloride Injection.
- Heparin Sodium 2,000 USP units per 1,000 mL (2 USP units per mL) in 0.9% Sodium Chloride Injection.

4 CONTRAINDICATIONS

The use of HEPARIN SODIUM IN 0.9% SODIUM CHLORIDE INJECTION is contraindicated in patients with the following conditions:

- Uncontrollable active bleeding state except when this is due to disseminated intravascular coagulation [see Warnings and Precautions (5.2)]
- History of heparin-induced thrombocytopenia (HIT) or heparin-induced thrombocytopenia and thrombosis (HITT) [see Warnings and Precautions (5.3)]
- Severe thrombocytopenia [see Warnings and Precautions (5.3, 5.4)]
- Known hypersensitivity to heparin or pork products (e.g., anaphylactoid reactions) [see Warnings and Precautions (5.5) and Adverse Reactions (6.1)]

5 WARNINGS AND PRECAUTIONS

5.1 Fatal Medication Errors

Do not use this product as a “catheter lock flush” product. Heparin is supplied in various strengths. Fatal hemorrhages have occurred due to medication errors. Carefully examine all heparin products to confirm the correct container choice prior to administration of the drug.

5.2 Hemorrhage

Hemorrhage, including fatal events, has occurred in patients receiving HEPARIN SODIUM. Avoid using heparin in the presence of major bleeding, except when the benefits of heparin therapy outweigh the potential risks.

Hemorrhage can occur at virtually any site in patients receiving heparin. Adrenal hemorrhage (with resultant acute adrenal insufficiency), ovarian hemorrhage, and retroperitoneal hemorrhage have occurred during anticoagulant therapy with heparin [see Adverse Reactions (6.1)]. A higher incidence of bleeding has been reported in patients, particularly women, over 60 years of age [see Clinical Pharmacology (12.3)]. An unexplained fall in hematocrit or fall in blood pressure should lead to serious consideration of a hemorrhagic event.

Use heparin sodium with caution in disease states in which there is increased risk of hemorrhage, including:

- Cardiovascular — Subacute bacterial endocarditis. Severe hypertension.
- Surgical — During and immediately following (a) spinal tap or spinal anesthesia or (b) major surgery, especially involving the brain, spinal cord or eye.
- Hematologic — Conditions associated with increased bleeding tendencies, such as hemophilia, thrombocytopenia and some vascular purpuras.
- Patients with hereditary antithrombin III deficiency receiving concurrent antithrombin III therapy — The anticoagulant effect of heparin is enhanced by concurrent treatment with antithrombin III (human) in patients with hereditary antithrombin III deficiency. To reduce the risk of bleeding, reduce the heparin dose during concomitant treatment with antithrombin III (human).
- Gastrointestinal — Ulcerative lesions and continuous tube drainage of the stomach or small intestine.
- Other — Menstruation, liver disease with impaired hemostasis.

5.3 Heparin-Induced Thrombocytopenia (HIT) and Heparin-Induced Thrombocytopenia and Thrombosis (HITT)

HIT is a serious immune-mediated reaction resulting from irreversible aggregation of platelets. HIT occurs in patients treated with heparin and is due to the development of antibodies to a platelet Factor 4-heparin complex that induce in vivo platelet aggregation. HIT may progress to the development of venous and arterial thromboses, a condition known as HITT. Thrombotic events may also be the initial presentation for HIT. These serious thromboembolic events include deep vein thrombosis, pulmonary embolism, cerebral vein thrombosis, limb ischemia, stroke, myocardial infarction, thrombus formation on a prosthetic cardiac valve, mesenteric thrombosis, renal arterial thrombosis, skin necrosis, gangrene of the extremities that may lead to amputation, and possibly death.

Once HIT or HITT is diagnosed or strongly suspected, discontinue all heparin sources (including heparin flushes) and use an alternative anticoagulant.

Immune-mediated HIT is diagnosed based on clinical findings supplemented by laboratory tests confirming the presence of antibodies to heparin, or platelet activation induced by heparin. Obtain platelet counts at baseline and periodically during heparin administration. A drop in platelet count greater than 50% from baseline is considered indicative of HIT. Platelet counts begin to fall 5 to 10 days after exposure to heparin in heparin–naive individuals and reach a threshold by days 7 to 14. In contrast, “rapid onset” HIT can occur very quickly (within 24 hours following heparin initiation), especially in patients with a recent exposure to heparin (i.e., previous 3 months).

Thrombosis development shortly after documenting thrombocytopenia is a characteristic finding in almost half of all patients with HIT.

Monitor thrombocytopenia of any degree closely. If the platelet count falls below 100,000/mm^3 or if recurrent thrombosis develops, promptly discontinue heparin, evaluate for HIT and HITT, and, if necessary, administer an alternative anticoagulant.

HIT or HITT can occur up to several weeks after the discontinuation of heparin therapy. Patients presenting with thrombocytopenia or thrombosis after discontinuation of heparin should be evaluated for HIT or HITT.

5.4 Thrombocytopenia

Thrombocytopenia has been reported to occur in patients receiving heparin with a reported incidence of up to 30%. It can occur 2 to 20 days (average 5 to 9) following the onset of heparin therapy. Obtain platelet counts before and periodically during heparin therapy. Monitor thrombocytopenia of any degree closely. If the count falls below 100,000/mm^3 or if recurrent thrombosis develops, promptly discontinue heparin, evaluate for HIT and HITT, and, if necessary, administer an alternative anticoagulant [see Warnings and Precautions (5.3)].

5.5 Hypersensitivity Reactions

Hypersensitivity reactions with chills, fever and urticaria as the most usual manifestations and also asthma, rhinitis, lacrimation, and anaphylactoid reactions have been reported. Patients with documented hypersensitivity to heparin should be given the drug only in clearly life-threatening situations. [see Adverse Reactions (6.1)].

Because Heparin Sodium in 0.9% Sodium Chloride Injection is derived from animal tissue, monitor for signs and symptoms of hypersensitivity when it is used in patients with a history of allergy to pork products.

5.6 Heparin Resistance

Increased resistance to heparin is frequently encountered in fever, thrombosis, thrombophlebitis, infections with thrombosing tendencies, myocardial infarction, cancer, in postsurgical patients, and patients with anti-thrombin deficiency. Consider measurement of anti-thrombin levels if heparin resistance is suspected. Monitor coagulation tests frequently in such patients. It may be necessary to adjust the dose of heparin based on coagulation test monitoring, such as anti-Factor Xa levels and/or partial thromboplastin time.

5.7 Hyperkalemia

Heparin can suppress adrenal secretion of aldosterone leading to hyperkalemia, particularly in patients with diabetes mellitus, chronic renal failure, pre-existing metabolic acidosis, a raised plasma potassium, or taking potassium sparing drugs. The risk of hyperkalemia appears to increase with duration of therapy but is usually reversible upon discontinuation of heparin.

Measure plasma potassium in patients at risk of hyperkalemia before starting heparin therapy and periodically in all patients treated for more than 5 days or earlier as deemed fit by the clinician.

5.8 Elevations of Serum Aminotransferases

Significant elevations of aspartate aminotransferase (AST) and alanine aminotransferase (ALT) levels have occurred in patients who have received heparin. Elevation of these enzymes in patients receiving heparin should be interpreted with caution. These elevations typically resolve upon heparin discontinuation.

5.9 Laboratory Tests

Periodic platelet counts, hematocrits, and tests for occult blood in stool are recommended during the entire course of heparin therapy, regardless of the route of administration.

6 ADVERSE REACTIONS

The following serious adverse reactions are described elsewhere in the labeling:

- Hemorrhage [see Warnings and Precautions (5.2)]

- Heparin-Induced Thrombocytopenia and Heparin-Induced Thrombocytopenia and Thrombosis [see Warnings and Precautions (5.3)]
- Thrombocytopenia [see Warnings and Precautions (5.4)]
- Hypersensitivity Reactions [see Warnings and Precautions (5.5)]
- Heparin Resistance [see Warnings and Precautions (5.6)]
- Hyperkalemia [see Warnings and Precautions (5.7)]
- Elevations of Serum Aminotransferases [see Warnings and Precautions (5.8)]

6.1 Postmarketing Experience

The following adverse reactions have been identified during post-approval use of heparin sodium. Because these reactions are reported voluntarily from a population of uncertain size, it is not always possible to reliably estimate their frequency.

- Hemorrhage – Hemorrhage is the chief complication that may result from heparin therapy [see Warnings and Precautions (5.2)]. An overly prolonged clotting time or minor bleeding during therapy can usually be controlled by withdrawing the drug [see Overdosage (10)]. Gastrointestinal or urinary tract bleeding during anticoagulant therapy may indicate the presence of an underlying occult lesion. Bleeding can occur at any site but certain specific hemorrhagic complications may be difficult to detect:
  - Adrenal hemorrhage, with resultant acute adrenal insufficiency, has occurred with heparin therapy, including fatal cases.
  - Ovarian (corpus luteum) hemorrhage developed in a number of women of reproductive age receiving short- or long-term anticoagulant therapy.
  - Retroperitoneal hemorrhage.
- Vascular Disorders – Contusion, Vasospastic reactions (including episodes of painful, ischemic, and cyanosed limbs).
- HIT and HITT, including delayed onset cases, and Thrombocytopenia – [see Warnings and Precautions (5.3 and 5.4)]
- Histamine-like reactions – Such reactions have been observed at the site of injections. Necrosis of the skin has been reported at the site of subcutaneous injection of heparin, occasionally requiring skin grafting.
- Hypersensitivity – Generalized hypersensitivity reactions have been reported with chills, fever, and urticaria as the most usual manifestations, and asthma, rhinitis, lacrimation, headache, nausea and vomiting, and anaphylactoid reactions, including shock, occurring more rarely. Itching and burning, especially on the plantar site of the feet, may occur [see Warnings and Precautions (5.5)].
- Musculoskeletal, Connective Tissue and Bone Disorders – Osteoporosis with long-term administration of heparin.
- Metabolism and Nutrition Disorders – Hyperkalemia.
- General Disorders and Administration Site Conditions – Erythema, mild pain, ulceration.
- Elevations of serum aminotransferases – Significant elevations of aspartate aminotransferase (AST) and alanine aminotransferase (ALT) levels have occurred in patients who have received heparin.
- Others – Cutaneous necrosis after systemic administration, delayed transient alopecia, priapism, and rebound hyperlipemia on discontinuation of heparin sodium have also been reported.

7 DRUG INTERACTIONS

7.1 Oral Anticoagulants

Heparin sodium may prolong the one-stage prothrombin time. Therefore, when heparin sodium is given with dicumarol or warfarin sodium, a period of at least 5 hours after the last intravenous dose or 24 hours after the last subcutaneous dose should elapse before blood is drawn if a valid prothrombin time is to be obtained.

7.2 Platelet Inhibitors

Drugs such as NSAIDS (including acetylsalicylic acid, ibuprofen, indomethacin, and celecoxib), dextran, phenylbutazone, thienopyridines, dipyridamole, hydroxychloroquine, glycoprotein IIv/IIa antagonists (including abciximab, eptifibatide, and tirofiban), and others that interfere with platelet-aggregation reactions (the main hemostatic defense of heparinized patients) may induce bleeding and should be used with caution in patients receiving heparin sodium. To reduce the risk of bleeding, a reduction in the dose of antiplatelet agent or heparin is recommended.

7.3 Other Medications that May Interfere with Heparin

Digitalis, tetracyclines, nicotine or antihistamines may partially counteract the anticoagulant action of heparin sodium. Intravenous nitroglycerin administered to heparinized patients may result in a decrease of the partial thromboplastin time with subsequent rebound effect upon discontinuation of nitroglycerin. Careful monitoring of partial thromboplastin time and adjustment of heparin dosage are recommended during coadministration of heparin and intravenous nitroglycerin.

Antithrombin III (human) – The anticoagulant effect of heparin is enhanced by concurrent treatment with antithrombin III (human) in patients with hereditary antithrombin III deficiency. To reduce the risk of bleeding, a reduced dosage of heparin is recommended during treatment with antithrombin III (human).

8 USE IN SPECIFIC POPULATIONS

8.1 Pregnancy

Risk Summary

In published reports, heparin exposure during pregnancy did not show evidence of an increased risk of adverse maternal or fetal outcomes in humans. No teratogenicity was observed in animal reproduction studies with administration of heparin sodium to pregnant rats and rabbits during organogenesis at doses, approximately 2777 times the recommended human dose (MRHD) for maintenance of catheter patency of heparin [see Data]. In pregnant animals, doses up to 2777 times higher than the human daily dose of heparin resulted in increased resorptions. Consider the benefits and risks of HEPARIN SODIUM IN 0.9% SODIUM CHLORIDE INJECTION to a pregnant woman and possible risks to the fetus when prescribing HEPARIN SODIUM IN 0.9% SODIUM CHLORIDE INJECTION.

The estimated background risk of major birth defects and miscarriage for the indicated population is unknown. In the U.S. general population, the estimated background risk of major birth defects and miscarriage in clinically recognized pregnancies is 2-4% and 15-20%, respectively.

Data

Human Data

The maternal and fetal outcomes associated with uses of heparin via various dosing methods and administration routes during pregnancy have been investigated in numerous studies. These studies generally reported normal deliveries with no maternal or fetal bleeding and no other complications.

Animal Data

In a published study conducted in rats and rabbits, pregnant animals received heparin intravenously during organogenesis at a dose of 10,000 USP units/kg/day, approximately 2777 times the human daily dose. The number of early resorptions increased in both species. There was no evidence of teratogenic effects.

8.2 Lactation

Risk Summary

There is no information regarding the presence of HEPARIN SODIUM IN 0.9% SODIUM CHLORIDE INJECTION in human milk, the effects on the breastfed infant, or the effects on milk production. Due to its large molecular weight, heparin is not likely to be excreted in human milk, and any heparin in milk would not be orally absorbed by a nursing infant. The developmental and health benefits of breastfeeding should be considered along with the mother’s clinical need for HEPARIN SODIUM IN 0.9% SODIUM CHLORIDE INJECTION and any potential adverse effects on the breastfed infant from HEPARIN SODIUM IN 0.9% SODIUM CHLORIDE INJECTION or from the underlying maternal condition [see Use in Specific Populations (8.4)].

8.4 Pediatric Use

There are no adequate and well controlled studies on heparin use in pediatric patients.

8.5 Geriatric Use

There are limited adequate and well-controlled studies in patients 65 years and older. However, a higher incidence of bleeding has been reported in patients over 60 years of age, especially women [see Warnings and Precautions (5.2)].

10 OVERDOSAGE

An overdose requires immediate medical attention and treatment.

Symptoms

Bleeding is the chief sign of heparin overdosage. Easy bruising, petechial formations, nosebleeds, blood in urine or tarry stools may be the first signs or symptoms of a heparin overdose. In the event of symptomatic heparin overdose, consider stopping heparin infusion.

Treatment

Neutralization of heparin effect:

When clinical circumstances (bleeding) require reversal of heparinization, protamine sulfate (1% solution) by slow infusion will neutralize heparin sodium. No more than 50 mg should be administered, very slowly, in any 10 minute period. Each mg of protamine sulfate neutralizes approximately 100 USP Heparin units. The amount of protamine required decreases over time as heparin is metabolized. Although the metabolism of heparin is complex, it may, for the purpose of choosing a protamine dose, be assumed to have a half-life of about 30 minutes after intravenous injection.

Ideally, the dose required to neutralize the action of heparin should be guided by blood coagulation tests or calculated from a protamine neutralization test.

Because fatal reactions often resembling anaphylaxis have been reported, protamine sulfate should be given only when resuscitation techniques and treatment of anaphylactoid shock are readily available.

For additional information, consult the prescribing information for Protamine Sulfate Injection, USP.

Blood or plasma transfusions may be necessary; these dilute but do not neutralize heparin.

11 DESCRIPTION

Heparin is a heterogenous group of straight-chain anionic mucopolysaccharides, called glycosaminoglycans having anticoagulant properties. It is composed of polymers of alternating derivations of alpha-L-iduronic acid 2-sulfate (1), 2-deoxy-2-sulfamino-alpha-D-glucose 6-sulfate (2), beta-D-glucuronic acid (3), 2-acetamido-2-deoxy-alpha-D-glucose (4), and alpha-L-iduronic acid (5).

Structure of Heparin Sodium (representative subunits):

Heparin Sodium in 0.9% Sodium Chloride Injection is a sterile, single-dose, clear, nonpyrogenic solution prepared from Heparin Sodium USP (derived from porcine intestinal mucosa and standardized for use as an anticoagulant) in 0.9% Sodium Chloride Injection. It is to be administered by intravenous injection. The potency is determined by a biological assay using a USP reference standard based on units of heparin activity per milligram.

Each 100 mL contains 200 USP Units Heparin Sodium, 0.43 g Dibasic Sodium Phosphate•7H2O USP and 0.037 g Citric Acid Anhydrous USP as a buffer system, 0.9 g Sodium Chloride USP, and Water for Injection USP qs.

pH: 7.0 (6.8-7.2); Calculated Osmolarity: 360 mOsmol/liter

Concentration of Electrolytes (mEq/liter): Sodium 186; Chloride 154;
Phosphate (HPO) 32; Citrate 6

The plastic container is made from a multilayered film specifically developed for parenteral drugs. It contains no plasticizers and exhibits virtually no leachables. The solution contact layer is a rubberized copolymer of ethylene and propylene. The container is nontoxic and biologically inert. The container-solution unit is a closed system and is not dependent upon entry of external air during administration. The container is overwrapped to provide protection from the physical environment and to provide an additional moisture barrier when necessary.

The plastic container is not made with natural rubber latex, PVC or DEHP.

The closure system has two ports; the one for the administration set has a tamper evident plastic protector.

12 CLINICAL PHARMACOLOGY

12.1 Mechanism of Action

Heparin interacts with the naturally occurring plasma protein, Antithrombin III, to induce a conformational change, which markedly enhances the serine protease activity of Antithrombin III, thereby inhibiting the activated coagulation factors involved in the closing sequence, particularly Xa and IIa. Small amounts of heparin inhibit Factor Xa, and larger amounts inhibit thrombin (Factor IIa). Heparin also prevents the formation of a stable fibrin clot by inhibiting the activation of the fibrin stabilizing factor. Heparin does not have fibrinolytic activity; therefore, it will not lyse existing clots.

12.2 Pharmacodynamics

Various times (activated clotting time, activated partial thromboplastin time, prothrombin time, whole blood clotting time) are prolonged by full therapeutic doses of heparin; in most cases, they are not measurably affected by low doses of heparin. Bleeding time is usually unaffected by heparin.

12.3 Pharmacokinetics

Absorption

Heparin is not absorbed through the gastrointestinal tract and therefore administered via parenteral route. Peak plasma concentration and the onset of action are achieved immediately after intravenous administration.

Distribution

Heparin is highly bound to antithrombin, fibrinogens, globulins, serum proteases and lipoproteins. The volume of distribution is 0.07 L/kg.

Elimination

Metabolism

Heparin does not undergo enzymatic degradation.

Excretion

Heparin is mainly cleared from the circulation by liver and reticuloendothelial cells mediated uptake into extravascular space. Heparin undergoes biphasic clearance, a) rapid saturable clearance (zero order process due to binding to proteins, endothelial cells and macrophages) and b) slower first order elimination. Low doses of heparin are cleared mostly by a saturable, rapid, zero-order process. Slower first order elimination usually occurs with very high doses of heparin and is dependent on renal function. The plasma half-life is dose-dependent, and it ranges from 0.5 to 2 h.

Specific Populations

Geriatric Patients

Patients over 60 years of age, following similar doses of heparin, may have higher plasma levels of heparin and longer activated partial thromboplastin times (APTTs) compared with patients under 60 years of age [see Use in Specific Populations (8.5)].

Renal and Hepatic Impairment

The rate of clearance of unfractionated heparin may be decreased in patients with renal or hepatic impairment. Patients with renal or hepatic impairment, following similar doses of heparin may have higher plasma levels of heparin compared with patient with normal renal and hepatic function [see Warnings and Precautions (5.2)].

13 NONCLINICAL TOXICOLOGY

13.1 Carcinogenesis, Mutagenesis, Impairment of Fertility

Long term studies in animals to evaluate the carcinogenic potential, reproduction studies in animals to determine effects on fertility of males and females, and studies to determine mutagenic potential have not been conducted.

16 HOW SUPPLIED/STORAGE AND HANDLING

Heparin Sodium in 0.9% Sodium Chloride Injection is a clear solution and is supplied sterile and nonpyrogenic in single-dose EXCEL® Containers. The 1,000 mL containers are packaged 12 per case and 500 mL containers are packaged 24 per case.

NDC | REF | Concentration | Size
0264-9872-10 | P8721 | Heparin Sodium 1,000 USP units per 500 mL (2 USP units per mL) in 0.9% Sodium Chloride Injection | 500 mL
0264-9872-00 | P8720 | Heparin Sodium 2,000 USP units per 1,000 mL (2 USP units per mL) in 0.9% Sodium Chloride Injection | 1,000 mL

Exposure of pharmaceutical products to heat should be minimized. Avoid excessive heat. Protect from freezing. Store at 20°C to 25°C (68°F to 77°F). Excursions permitted to 15°C to 30°C (59°F to 86°F). [See USP Controlled Room Temperature.]

17 PATIENT COUNSELING INFORMATION

Hemorrhage

Inform patients that it may take them longer than usual to stop bleeding, that they may bruise and/or bleed more easily when they are treated with heparin, and that they should report any unusual bleeding or bruising to their physician. Hemorrhage can occur at virtually any site in patients receiving heparin. Fatal hemorrhages have occurred [see Warnings and Precautions (5.2)].

Prior to Surgery

Advise patients to inform physicians and dentists that they are receiving heparin before any surgery is scheduled [see Warnings and Precautions (5.2)].

Heparin-Induced Thrombocytopenia

Inform patients of the risk of heparin-induced thrombocytopenia (HIT). HIT may progress to the development of venous and arterial thromboses, a condition known as heparin-induced thrombocytopenia and thrombosis (HITT). HIT or HITT can occur up to several weeks after the discontinuation of heparin therapy [see Warnings and Precautions (5.3 and 5.4)].

Hypersensitivity

Inform patients that generalized hypersensitivity reactions have been reported. Necrosis of the skin has been reported at the site of subcutaneous injection of heparin [see Warnings and Precautions (5.5), Adverse Reactions (6.1)].

Other Medications

Because of the risk of hemorrhage, advise patients to inform their physicians and dentists of all medications they are taking, including non-prescription medications, and before starting any new medication [see Drug Interactions (7)].

Rx only

EXCEL is a registered trademark of B. Braun Medical Inc.

B. Braun Medical Inc.

Bethlehem, PA 18018-3524 USA

1-800-227-2862

Y36-003-067 LD-240-9

PRINCIPAL DISPLAY PANEL - 1000 mL Container Label

NDC 0264-9872-00

HEPARIN SODIUM in
0.9% Sodium Chloride Injection
2,000 USP units per 1000 mL
(2 USP units per mL)

LD-756-1 Y94-003-481

For Intravenous Use Only

Each 100 mL contains: Heparin Sodium USP
(porcine intestinal mucosa) 200 USP Heparin units;
Sodium Chloride USP 0.9 g;
Dibasic Sodium Phosphate•7H2O USP 0.43 g;
Citric Acid Anhydrous USP 0.037 g;
Water for Injection USP qs

Electrolytes (mEq/liter): Sodium 186; Chloride 154;
Phosphate (HPO) 32; Citrate 6

WARNING: Do not admix with other drugs.

Sterile. Single dose container. Discard unused portion.

Store at 20°C to 25°C (68°F to 77°F). Excursions permitted to 15°C to 30°C (59°F to 86°F). [See USP Controlled Room Temperature.] Avoid excessive heat. Protect from freezing. Recommended Dosage: see Prescribing Information. Do not remove overwrap until ready for use.

Not made with natural rubber latex, PVC or DEHP.

EXCEL is a registered trademark of B. Braun Medical Inc.

1000 mL EXCEL® CONTAINER

Rx only

REF P8720

B. Braun Medical Inc.
Bethlehem, PA 18018-3524 USA
1-800-227-2862
Prepared in USA. API from Spain.

Y94-003-480 LD-755-1

EXP

LOT

PRINCIPAL DISPLAY PANEL - 500 mL Container Label

NDC 0264-9872-10

HEPARIN SODIUM in
0.9% Sodium Chloride Injection
1,000 USP units per 500 mL
(2 USP units per mL)

LD-312-8 Y94-003-513

For Intravenous Use Only

Each 100 mL contains: Heparin Sodium USP
(porcine intestinal mucosa) 200 USP Heparin units;
Sodium Chloride USP 0.9 g;
Dibasic Sodium Phosphate•7H2O USP 0.43 g;
Citric Acid Anhydrous USP 0.037 g;
Water for Injection USP qs

Electrolytes (mEq/liter): Sodium 186; Chloride 154;
Phosphate (HPO) 32; Citrate 6

WARNING: Do not admix with other drugs.

Sterile. Single dose container. Discard unused portion.

Store at 20°C to 25°C (68°F to 77°F). Excursions permitted to 15°C to 30°C (59°F to 86°F). [See USP Controlled Room Temperature.] Avoid excessive heat. Protect from freezing. Recommended Dosage: see Prescribing Information. Do not remove overwrap until ready for use.

Not made with natural rubber latex, PVC or DEHP.

EXCEL is a registered trademark of B. Braun Medical Inc.

500 mL EXCEL® CONTAINER

Rx only

REF P8721

B. Braun Medical Inc.
Bethlehem, PA 18018-3524 USA
1-800-227-2862
Prepared in USA. API from Spain.

Y94-003-482 LD-311-6

EXP

LOT